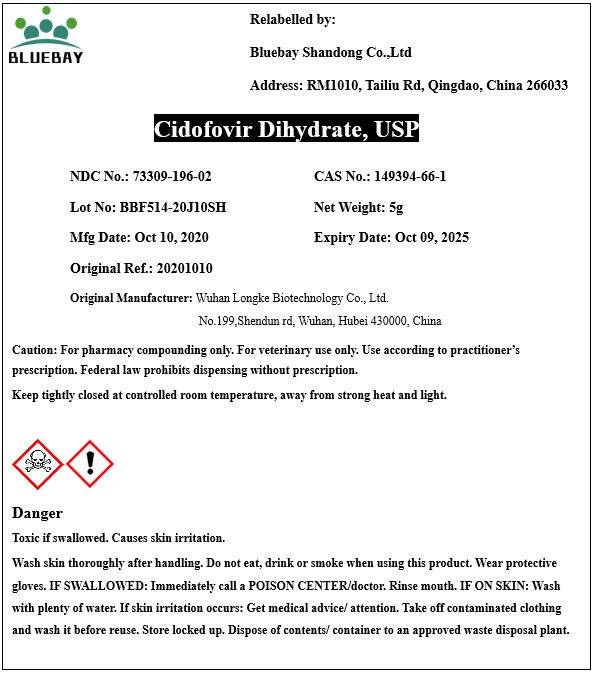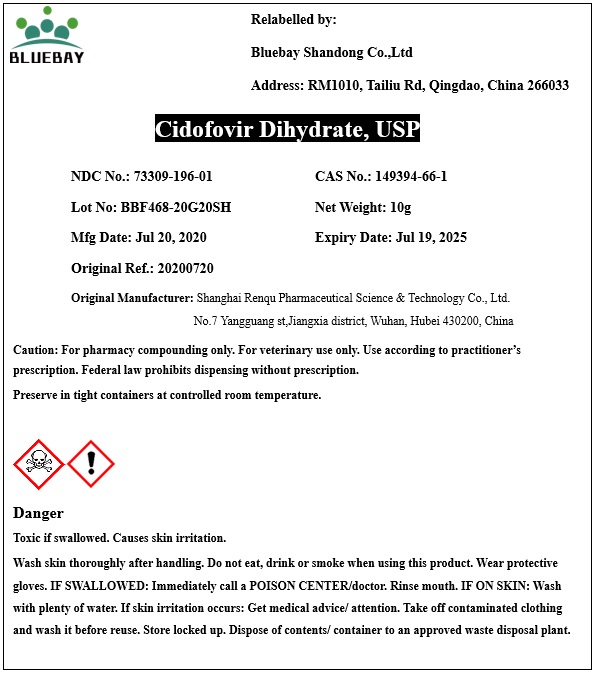 DRUG LABEL: Cidofovir Dihydrate
NDC: 73309-196 | Form: POWDER
Manufacturer: BLUEBAY SHANDONG CO.,LTD
Category: other | Type: BULK INGREDIENT
Date: 20201021

ACTIVE INGREDIENTS: CIDOFOVIR 1 g/1 g

Cidofovir Dihydrate